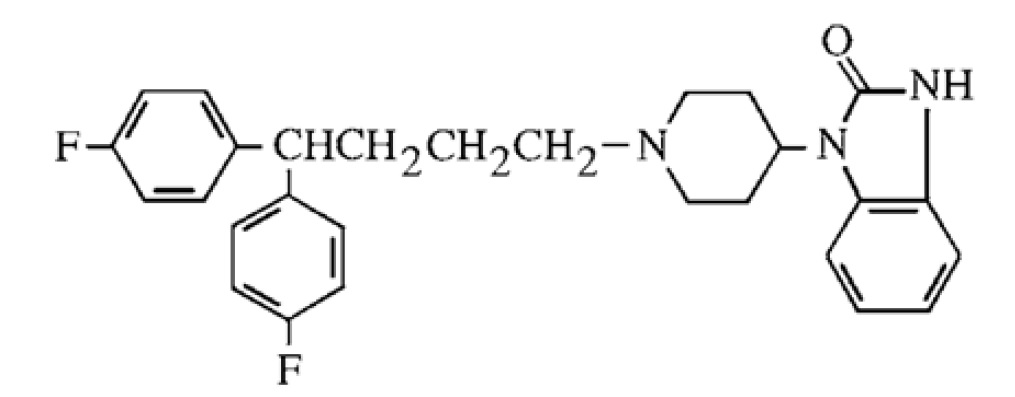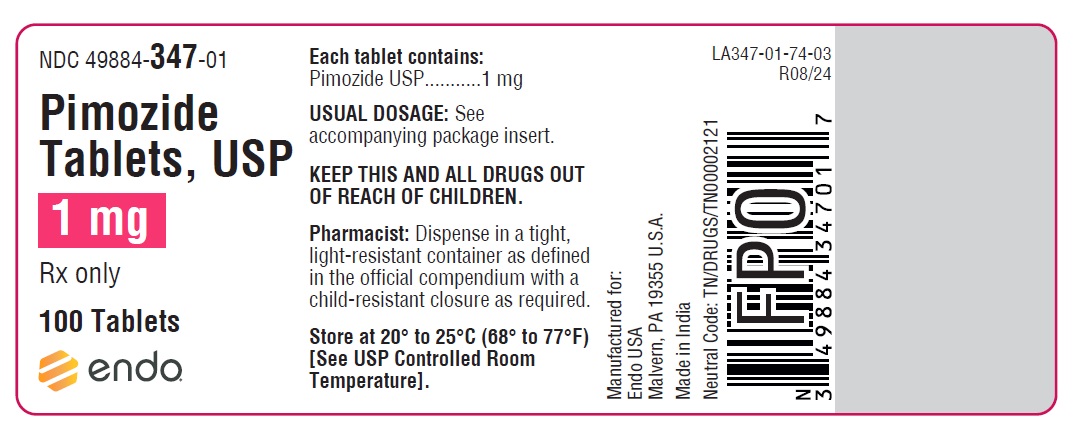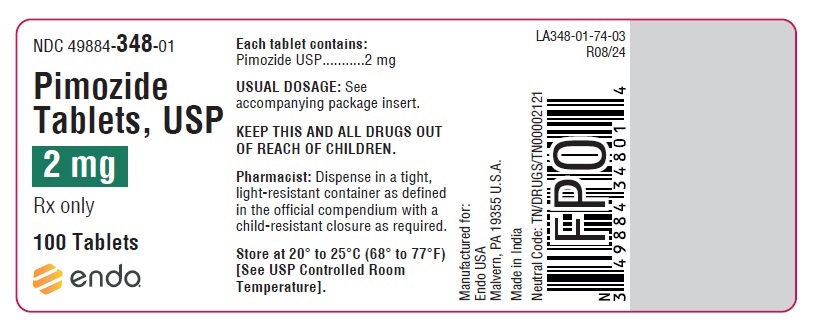 DRUG LABEL: Pimozide
NDC: 49884-347 | Form: TABLET
Manufacturer: Endo USA, Inc.
Category: prescription | Type: HUMAN PRESCRIPTION DRUG LABEL
Date: 20171125

ACTIVE INGREDIENTS: PIMOZIDE 1 mg/1 1
INACTIVE INGREDIENTS: ANHYDROUS LACTOSE; CALCIUM STEARATE; CELLULOSE, MICROCRYSTALLINE; STARCH, CORN

Pimozide Tablets, USP

DESCRIPTION

Pimozide is an orally active antipsychotic agent of the diphenyl-butylpiperidine series. The structural formula of pimozide, 1-[1-[4,4-bis(4-fluorophenyl)butyl]-4-piperidinyl]-1,3-dihydro-2H-benzimidazole-2-one is:

The solubility of pimozide in water is less than 0.01 mg/mL; it is slightly soluble in most organic solvents.

Each white pimozide tablet contains either 1 mg or 2 mg of pimozide and the following inactive ingredients: calcium stearate, microcrystalline cellulose, lactose anhydrous and corn starch.

CLINICAL PHARMACOLOGY

Pharmacodynamic Actions
Pimozide tablets, are an orally active antipsychotic drug product which shares with other antipsychotics the ability to blockade dopaminergic receptors on neurons in the central nervous system. Although its exact mode of action has not been established, the ability of pimozide to suppress motor and phonic tics in Tourette’s Disorder is thought to be a function of its dopaminergic blocking activity. However, receptor blockade is often accompanied by a series of secondary alterations in central dopamine metabolism and function which may contribute to both pimozide’s therapeutic and untoward effects. In addition, pimozide tablets, in common with other antipsychotic drugs, has various effects on other central nervous system receptor systems which are not fully characterized.

Metabolism and Pharmacokinetics

More than 50% of a dose of pimozide is absorbed after oral administration. Based on the pharmacokinetic and metabolic profile, pimozide appears to undergo significant first pass metabolism. Peak serum levels occur generally six to eight hours (range 4 to 12 hours) after dosing.

Pimozide is extensively metabolized, primarily by N-dealkylation in the liver. This metabolism is catalyzed mainly by the cytochrome P450 3A4 (CYP 3A4) enzymatic system and to a lesser extent, by cytochrome P450 1A2 (CYP 1A2) and cytochrome P450 2D6 (CYP 2D6). Two major metabolites have been identified, 1-(4-piperidyl)-2-benzimidazolinone and 4,4-bis(4-fluorophenyl) butyric acid. The antipsychotic activity of these metabolites is undetermined. The major route of elimination of pimozide and its metabolites is through the kidney.

The mean serum elimination half-life of pimozide in schizophrenic patients was approximately 55 hours. There was a 13-fold interindividual difference in the area under the serum pimozide level-time curve and an equivalent degree of variation in peak serum levels among patients studied. The significance of this is unclear since there are few correlations between plasma levels and clinical findings.

Effects of food and disease upon the absorption, distribution, metabolism and elimination of pimozide are not known. Effects of concomitant medication and genetic variations on pimozide metabolism are described in the CONTRAINDICATIONS and PRECAUTIONS sections.

INDICATIONS AND USAGE

Pimozide tablets, USP are indicated for the suppression of motor and phonic tics in patients with Tourette’s Disorder who have failed to respond satisfactorily to standard treatment. Pimozide Tablets, USP are not intended as a treatment of first choice nor is it intended for the treatment of tics that are merely annoying or cosmetically troublesome. Pimozide Tablets, USP should be reserved for use in Tourette’s Disorder patients whose development and/or daily life function is severely compromised by the presence of motor and phonic tics.

Evidence supporting approval of pimozide tablets, USP for use in Tourette’s Disorder was obtained in two controlled clinical investigations which enrolled patients between the ages of 8 and 53 years. Most subjects in the two trials were 12 or older.

CONTRAINDICATIONS

1. Pimozide is contraindicated in the treatment of simple tics or tics other than those associated with Tourette’s Disorder.

2. Pimozide should not be used in patients taking drugs that may, themselves, cause motor and phonic tics (e.g., pemoline, methylphenidate and amphetamines) until such patients have been withdrawn from these drugs to determine whether or not the drugs, rather than Tourette’s Disorder, are responsible for the tics.

3. Because pimozide prolongs the QT interval of the electrocardiogram it is contraindicated in patients with congenital long QT syndrome, patients with a history of cardiac arrhythmias, patients taking other drugs which prolong the QT interval of the electrocardiogram or patients with known hypokalemia or hypomagnesemia (see also PRECAUTIONS - DRUG INTERACTIONS).

4. Pimozide is contraindicated in patients with severe toxic central nervous system depression or comatose states from any cause.

5. Pimozide is contraindicated in patients with hypersensitivity to it. As it is not known whether cross-sensitivity exists among the antipsychotics, pimozide should be used with appropriate caution in patients who have demonstrated hypersensitivity to other antipsychotic drugs.

6. Ventricular arrhythmias have been rarely associated with the use of macrolide antibiotics in patients with prolonged QT intervals, as might be produced by pimozide. Specifically, two sudden deaths have been reported when clarithromycin was added to ongoing pimozide therapy. Furthermore, some evidence suggests that pimozide is metabolized partly by the enzyme system cytochrome P450 3A4 (CYP 3A4). Macrolide antibiotics are inhibitors of CYP 3A4, and thus could potentially impede pimozide metabolism. For these reasons, pimozide is contraindicated in patients receiving the macrolide antibiotics clarithromycin, erythromycin, azithromycin, dirithromycin, and troleandomycin.

7. Concomitant use in patients taking Celexa or Lexapro is contraindicated (see PRECAUTIONS - DRUG INTERACTIONS - Pimozide and Celexa).

8. Clinical drug interaction studies have demonstrated that pimozide is also metabolized by CYP 2D6. Concomitant use of pimozide with paroxetine and other strong CYP 2D6 inhibitors is contraindicated (See PRECAUTIONS – DRUG INTERACTIONS).

9. Concomitant use of pimozide in patients taking sertraline is contraindicated (See PRECAUTIONS – DRUG INTERACTIONS).

Because azole antifungal agents are also inhibitors of the CYP 3A4 enzymes and thus may likewise impair pimozide metabolism, pimozide is contraindicated in patients receiving the azole antifungal agents itraconazole and ketoconazole.

Similarly, protease inhibitor drugs are also inhibitors of CYP 3A4, and thus pimozide is contraindicated in patients receiving protease inhibitors such as ritonavir, saquinovir, indinavir, and nelfinavir. (See PRECAUTIONS - DRUG INTERACTIONS.)

Nefazodone is a potent inhibitor of CYP 3A4, and its concomitant use with pimozide is also contraindicated.

Other drugs that are relatively less potent inhibitors of CYP 3A4 should also be avoided, in view of the risks: e.g., zileuton, fluvoxamine.

WARNINGS

The use of pimozide in the treatment of Tourette’s Disorder involves different risk/benefit considerations than when antipsychotic drugs are used to treat other conditions. Consequently, a decision to use pimozide should take into consideration the following (see also PRECAUTIONS - Information for Patients).

Tardive Dyskinesia

A syndrome consisting of potentially irreversible, involuntary, dyskinetic movements may develop in patients treated with antipsychotic drugs. Although the prevalence of the syndrome appears to be highest among the elderly, especially elderly women, it is impossible to rely upon prevalence estimates to predict, at the inception of antipsychotic treatment, which patients are likely to develop the syndrome. Whether antipsychotic drug products differ in their potential to cause tardive dyskinesia is unknown.

Both the risk of developing tardive dyskinesia and the likelihood that it will become irreversible are believed to increase as the duration of treatment and the total cumulative dose of antipsychotic drugs administered to the patient increase. However, the syndrome can develop, although much less commonly, after relatively brief treatment periods at low doses.

There is no known treatment for established cases of tardive dyskinesia, although the syndrome may remit, partially or completely, if antipsychotic treatment is withdrawn. Antipsychotic treatment itself, however, may suppress (or partially suppress) the signs and symptoms of the syndrome and thereby may possibly mask the underlying process. The effect that symptomatic suppression has upon the long-term course of the syndrome is unknown.

Given these considerations, antipsychotic drugs should be prescribed in a manner that is most likely to minimize the occurrence of tardive dyskinesia. Chronic antipsychotic treatment should generally be reserved for patients who suffer from a chronic illness, that 1) is known to respond to antipsychotic drugs, and, 2) for whom alternative, equally effective, but potentially less harmful treatments are not available or appropriate. In patients who do require chronic treatment, the smallest dose and the shortest duration of treatment producing a satisfactory clinical response should be sought. The need for continued treatment should be reassessed periodically.

If signs and symptoms of tardive dyskinesia appear in a patient on antipsychotics, drug discontinuation should be considered. However, some patients may require treatment despite the presence of the syndrome.

(For further information about the description of tardive dyskinesia and its clinical detection, please refer to ADVERSE REACTIONS and PRECAUTIONS - Information for Patients.)

Neuroleptic Malignant Syndrome (NMS)

A potentially fatal symptom complex sometimes referred to as Neuroleptic Malignant Syndrome (NMS) has been reported in association with antipsychotic drugs. Clinical manifestations of NMS are hyperpyrexia, muscle rigidity, altered mental status (including catatonic signs) and evidence of autonomic instability (irregular pulse or blood pressure, tachycardia, diaphoresis, and cardiac dysrhythmias). Additional signs may include elevated creatine phosphokinase, myoglobinuria (rhabdomyolysis) and acute renal failure.

The diagnostic evaluation of patients with this syndrome is complicated. In arriving at a diagnosis, it is important to identify cases where the clinical presentation includes both serious medical illness (e.g., pneumonia, systemic infection, etc.) and untreated or inadequately treated extrapyramidal signs and symptoms (EPS). Other important considerations in the differential diagnosis include central anticholinergic toxicity, heat stroke, drug fever and primary central nervous system (CNS) pathology.

The management of NMS should include 1) immediate discontinuation of antipsychotic drugs and other drugs not essential to concurrent therapy, 2) intensive symptomatic treatment and medical monitoring, and 3) treatment of any concomitant serious medical problems for which specific treatments are available. There is no general agreement about specific pharmacological treatment regimens for uncomplicated NMS.

If a patient requires antipsychotic drug treatment after recovery from NMS, the potential reintroduction of drug therapy should be carefully considered. The patient should be carefully monitored, since recurrences of NMS have been reported.

Hyperpyrexia, not associated with the above symptom complex, has been reported with other antipsychotic drugs.

Other

Sudden, unexpected deaths have occurred in experimental studies of conditions other than Tourette’s Disorder. These deaths occurred while patients were receiving dosages in the range of 1 mg per kg. One possible mechanism for such deaths is prolongation of the QT interval predisposing patients to ventricular arrhythmia. An electrocardiogram should be performed before pimozide treatment is initiated and periodically thereafter, especially during the period of dose adjustment.

Pimozide may have a tumorigenic potential. Based on studies conducted in mice, it is known that pimozide can produce a dose-related increase in pituitary tumors. The full significance of this finding is not known, but should be taken into consideration in the physician’s and patient’s decisions to use this drug product. This finding should be given special consideration when the patient is young and chronic use of pimozide is anticipated (see PRECAUTIONS - Carcinogenesis, Mutagenesis, Impairment of Fertility).

PRECAUTIONS

Leukopenia, Neutropenia and Agranulocytosis

Class Effect: In clinical trial and/or postmarketing experience, events of leukopenia/neutropenia and agranulocytosis have been reported temporally related to antipsychotic agents.

Possible risk factors for leukopenia/neutropenia include preexisting low white blood cell count (WBC) and history of drug induced leukopenia/neutropenia. Patients with a history of a clinically significant low WBC or drug induced leukopenia/neutropenia should have their complete blood count (CBC) monitored frequently during the first few months of therapy and discontinuation of pimozide should be considered at the first sign of a clinically significant decline in WBC in the absence of other causative factors.

Patients with clinically significant neutropenia should be carefully monitored for fever or other symptoms or signs of infection and treated promptly if such symptoms or signs occur. Patients with severe neutropenia (absolute neutrophil count <1000/mm^3) should discontinue pimozide and have their WBC followed until recovery.

General

Pimozide may impair the mental and/or physical abilities required for the performance of potentially hazardous tasks, such as driving a car or operating machinery, especially during the first few days of therapy.

Pimozide produces anticholinergic side effects and should be used with caution in individuals whose conditions may be aggravated by anticholinergic activity.
Pimozide should be administered cautiously to patients with impairment of liver or kidney function, because it is metabolized by the liver and excreted by the kidneys.
Antipsychotics should be administered with caution to patients receiving anticonvulsant medication, with a history of seizures, or with EEG abnormalities, because they may lower the convulsive threshold. If indicated, adequate anticonvulsant therapy should be maintained concomitantly.

Information for Patients

Treatment with pimozide tablets, USP exposes the patient to serious risks. A decision to use pimozide tablets, USP chronically in Tourette’s Disorder is one that deserves full consideration by the patient (or patient’s family) as well as by the treating physician. Because the goal of treatment is symptomatic improvement, the patient’s view of the need for treatment and assessment of response are critical in evaluating the impact of therapy and weighing its benefits against the risks. Since the physician is the primary source of information about the use of a drug in any disease, it is recommended that the following information be discussed with patients and/or their families.

Pimozide tablets, are intended only for use in patients with Tourette’s Disorder whose symptoms are severe and who cannot tolerate, or who do not respond to HALDOL® (haloperidol).

Given the likelihood that a proportion of patients exposed chronically to antipsychotics will develop tardive dyskinesia, it is advised that all patients in whom chronic use is contemplated be given, if possible, full information about this risk. The decision to inform patients and/or their guardians must obviously take into account the clinical circumstances and the competency of the patient to understand the information provided.

There is limited information available on the use of pimozide tablets, USP in children under 12 years of age.

The information available on pimozide tablets, USP from foreign marketing experience and from U.S. clinical trials indicates that pimozide tablets, have a side effect profile similar to that of other antipsychotic drugs. Patients should be informed that all types of side effects associated with the use of antipsychotics may be associated with the use of pimozide tablets.

In addition, sudden, unexpected deaths have occurred in patients taking high doses of pimozide tablets, USP for conditions other than Tourette’s Disorder. These deaths may have been the result of an effect of pimozide upon the heart. Therefore, patients should be instructed not to exceed the prescribed dose of pimozide tablets, USP and they should realize the need for the initial ECG and for follow-up ECGs during treatment.

Also, pimozide, at a dose about 15 times that given humans, caused an increase in the number of benign tumors of the pituitary gland in female mice. It is not possible to say how important this is. Similar tumors were not seen in rats given pimozide, nor at lower doses in mice, which is reassuring. However, any such finding must be considered to suggest a possible risk of long term use of the drug.
Because substances in grapefruit juice may inhibit the metabolism of pimozide by CYP 3A4, patients should be advised to avoid grapefruit juice.

Laboratory Tests

An ECG should be done at baseline and periodically thereafter throughout the period of dose adjustment. Any indication of prolongation of QTc interval beyond an absolute limit of 0.47 seconds (children) or 0.52 seconds (adults), or more than 25% above the patient’s original baseline should be considered a basis for stopping further dose increase (see CONTRAINDICATIONS) and considering a lower dose.

Since hypokalemia has been associated with ventricular arrhythmias, potassium insufficiency, secondary to diuretics, diarrhea, or other cause, should be corrected before pimozide therapy is initiated and normal potassium maintained during therapy.

DRUG INTERACTIONS

Because pimozide prolongs the QT interval of the electrocardiogram, an additive effect on QT interval would be anticipated if administered with other drugs, such as phenothiazines, tricyclic antidepressants or antiarrhythmic agents, which prolong the QT interval. Accordingly, pimozide should not be given with dofetilide, sotalol, quinidine, other Class Ia and III anti-arrhythmics, mesoridazine, thioridazine, chlorpromazine, droperidol, sparfloxacin, gatifloxacin, moxifloxacin, halofantrine, mefloquine, pentamidine, arsenic trioxide, levomethadyl acetate, dolasetron mesylate, probucol, tacrolimus, ziprasidone, or other drugs that have demonstrated QT prolongation as one of their pharmacodynamic effects. Also, the use of macrolide antibiotics in patients with prolonged QT intervals has been rarely associated with ventricular arrhythmias. Such concomitant administration should not be undertaken (see CONTRAINDICATIONS).

Since pimozide is partly metabolized via CYP 3A4, it should not be administered concomitantly with inhibitors of this metabolic system, such as azole antifungal agents and protease inhibitor drugs (see CONTRAINDICATIONS).

Pimozide and Celexa: In a controlled study, a single dose of pimozide 2 mg coadministered with racemic citalopram 40 mg given once daily for 11 days was associated with a mean increase in QTc values of approximately 10 msec compared to pimozide given alone. Racemic citalopram did not alter the mean AUC or Cmax of pimozide. The mechanism of this pharmacodynamic interaction is not known. Concomitant use of Pimozide and Celexa or Lexapro is contraindicated (See CONTRAINDICATIONS).

CYP 2D6 inhibitors: In healthy subjects, co-administration of pimozide 2 mg (single dose) and paroxetine 60 mg resulted in a 151% increase in pimozide AUC and a 62% increase in pimozide Cmax compared to pimozide administered alone. The increase in pimozide AUC and Cmax is related to the CYP 2D6 inhibitory properties of paroxetine. Concomitant use of pimozide and paroxetine or other strong CYP 2D6 inhibitors are contraindicated (see CONTRAINDICATIONS).

As CYP 1A2 may also contribute to the metabolism of pimozide, prescribers should be aware of the theoretical potential for drug interactions with inhibitors of this enzymatic system.

Pimozide may be capable of potentiating CNS depressants, including analgesics, sedatives, anxiolytics, and alcohol.

Rare case reports have suggested possible additive effects of pimozide and fluoxetine leading to bradycardia.

Concomitant administration of pimozide and sertraline should be contraindicated (See CONTRAINDICATIONS).

Pharmacogenomics Individuals with genetic variations resulting in poor CYP 2D6 metabolism (approximately 5 to 10% of the population) exhibit higher pimozide concentrations than extensive CYP 2D6 metabolizers. The concentrations observed in poor CYP 2D6 metabolizers are similar to those seen with strong CYP 2D6 inhibitors such as paroxetine. The time to achieve steady-state pimozide concentrations is expected to be longer (approximately 2 weeks) in poor CYP 2D6 metabolizers because of the prolonged half-life. Alternative dosing strategies are recommended in patients who are genetically poor CYP 2D6 metabolizers (see DOSAGE and ADMINISTRATION).

Interaction with Food

Patients should avoid grapefruit juice because it may inhibit the metabolism of pimozide by CYP 3A4.

Carcinogenesis, Mutagenesis, Impairment of Fertility

Carcinogenicity studies were conducted in mice and rats. In mice, pimozide causes a dose-related increase in pituitary and mammary tumors.

When mice were treated for up to 18 months with pimozide, pituitary gland changes developed in females only. These changes were characterized as hyperplasia at doses approximating the human dose and adenoma at doses about fifteen times the maximum recommended human dose on a mg per kg basis. The mechanism for the induction of pituitary tumors in mice is not known.

Mammary gland tumors in female mice were also increased, but these tumors are expected in rodents treated with antipsychotic drugs which elevate prolactin levels. Chronic administration of an antipsychotic also causes elevated prolactin levels in humans. Tissue culture experiments indicate that approximately one-third of human breast cancers are prolactin-dependent in vitro, a factor of potential importance if the prescription of these drugs is contemplated in a patient with a previously detected breast cancer. Although disturbances such as galactorrhea, amenorrhea, gynecomastia, and impotence have been reported with antipsychotic drugs, the clinical significance of elevated serum prolactin levels is unknown for most patients. Neither clinical studies nor epidemiologic studies conducted to date have shown an association between chronic administration of these drugs and mammary tumorigenesis. The available evidence, however, is considered too limited to be conclusive at this time.

In a 24-month carcinogenicity study in rats, animals received up to 50 times the maximum recommended human dose. No increased incidence of overall tumors or tumors at any site was observed in either sex. Because of the limited number of animals surviving this study, the meaning of these results is unclear.

Pimozide did not have mutagenic activity in the Ames test with four bacterial test strains, in the mouse dominant lethal test or in the micronucleus test in rats.

Reproduction studies in animals were not adequate to assess all aspects of fertility. Nevertheless, female rats administered pimozide had prolonged estrus cycles, an effect also produced by other antipsychotic drugs.

Pregnancy

Teratogenic Effects: Reproduction studies performed in rats and rabbits at oral doses up to 8 times the maximum human dose did not reveal evidence of teratogenicity. In the rat, however, this multiple of the human dose resulted in decreased pregnancies and in the retarded development of fetuses. These effects are thought to be due to an inhibition or delay in implantation which is also observed in rodents administered other antipsychotic drugs. In the rabbit, maternal toxicity, mortality, decreased weight gain, and embryotoxicity including increased resorptions were dose-related. Because animal reproduction studies are not always predictive of human response, pimozide should be given to a pregnant woman only if the potential benefits of treatment clearly outweigh the potential risks.

Nonteratogenic effects. Neonates exposed to antipsychotic drugs, during the third trimester of pregnancy are at risk for extrapyramidal and/or withdrawal symptoms following delivery. There have been reports of agitation, hypertonia, hypotonia, tremor, somnolence, respiratory distress and feeding disorder in these neonates. These complications have varied in severity; while in some cases symptoms have been self-limited, in other cases neonates have required intensive care unit support and prolonged hospitalization.

Pimozide should be used during pregnancy only if the potential benefit justifies the potential risk to the fetus.

Labor and Delivery

This drug has no recognized use in labor or delivery.

Nursing Mothers

It is not known whether pimozide is excreted in human milk. Because many drugs are excreted in human milk and because of the potential for tumorigenicity and unknown cardiovascular effects in the infant, a decision should be made whether to discontinue nursing or to discontinue the drug, taking into account the importance of the drug to the mother.

Pediatric Use

Although Tourette's Disorder most often has its onset between the ages of 2 and 15 years, information on the use and efficacy of pimozide in patients less than 12 years of age is limited. A 24-week open label study in 36 children between the ages of 2 and 12 demonstrated that pimozide has a similar safety profile in this age group as in older patients and there were no safety findings that would preclude its use in this age group.
Because its use and safety have not been evaluated in other childhood disorders, pimozide is not recommended for use in any condition other than Tourette’s Disorder.

ADVERSE REACTIONS

General

Extrapyramidal Reactions: Neuromuscular (extrapyramidal) reactions during the administration of pimozide have been reported frequently, often during the first few days of treatment. In most patients, these reactions involved Parkinson-like symptoms which, when first observed, were usually mild to moderately severe and usually reversible.

Other types of neuromuscular reactions (motor restlessness, dystonia, akathisia, hyperreflexia, opisthotonos, oculogyric crises) have been reported far less frequently. Severe extrapyramidal reactions have been reported to occur at relatively low doses. Generally the occurrence and severity of most extrapyramidal symptoms are dose-related since they occur at relatively high doses and have been shown to disappear or become less severe when the dose is reduced. Administration of antiparkinson drugs such as benztropine mesylate or trihexyphenidyl hydrochloride may be required for control of such reactions. It should be noted that persistent extrapyramidal reactions have been reported and that the drug may have to be discontinued in such cases.

Withdrawal Emergent Neurological Signs: Generally, patients receiving short term therapy experience no problems with abrupt discontinuation of antipsychotic drugs.

However, some patients on maintenance treatment experience transient dyskinetic signs after abrupt withdrawal. In certain of these cases the dyskinetic movements are indistinguishable from the syndrome described below under “Tardive Dyskinesia” except for duration. It is not known whether gradual withdrawal of antipsychotic drugs will reduce the rate of occurrence of withdrawal emergent neurological signs, but until further evidence becomes available, it seems reasonable to gradually withdraw use of pimozide.

Tardive Dyskinesia: Pimozide may be associated with persistent dyskinesias. Tardive dyskinesia, a syndrome consisting of potentially irreversible, involuntary, dyskinetic movements, may appear in some patients on long-term therapy or may occur after drug therapy has been discontinued. The risk appears to be greater in elderly patients on high-dose therapy, especially females. The symptoms are persistent and in some patients appear irreversible. The syndrome is characterized by rhythmical involuntary movements of tongue, face, mouth or jaw (e.g., protrusion of tongue, puffing of cheeks, puckering of mouth, chewing movements). Sometimes these may be accompanied by involuntary movements of extremities and the trunk.

There is no known effective treatment for tardive dyskinesia; antiparkinson agents usually do not alleviate the symptoms of this syndrome. It is suggested that all antipsychotic agents be discontinued if these symptoms appear. Should it be necessary to reinstitute treatment, or increase the dosage of the agent, or switch to a different antipsychotic agent, this syndrome may be masked.

It has been reported that fine vermicular movement of the tongue may be an early sign of tardive dyskinesia and if the medication is stopped at that time the syndrome may not develop.
Electrocardiographic Changes: Electrocardiographic changes have been observed in clinical trials of pimozide in Tourette’s Disorder and schizophrenia. These have included prolongation of the QT interval, flattening, notching and inversion of the T wave and the appearance of U waves. Sudden, unexpected deaths and grand mal seizure have occurred at doses above 20 mg/day.
Neuroleptic Malignant Syndrome: Neuroleptic malignant syndrome (NMS) has been reported with pimozide. (See WARNINGS for further information concerning NMS.)

Hyperpyrexia: Hyperpyrexia has been reported with other antipsychotic drugs.

CLINICAL TRIALS

The following adverse reaction tabulation was derived from 20 patients in a 6-week long placebo-controlled clinical trial of pimozide in Tourette’s Disorder.

Body System/ Adverse Reaction | Pimozide (N=20) | Placebo (N=20)
Body as a Whole
Headache | 1 | 2
Gastrointestinal
Dry Mouth | 5 | 1
Diarrhea | 1 | 0
Nausea | 0 | 2
Vomiting | 0 | 1
Constipation | 4 | 2
Eructations | 0 | 1
Thirsty | 1 | 0
Appetite increase | 1 | 0
Endocrine
Menstrual disorder | 0 | 1
Breast secretions | 0 | 1
Musculoskeletal
Muscle cramps | 0 | 1
Muscle tightness | 3 | 0
Stooped posture | 2 | 0
CNS
Drowsiness | 7 | 3
Sedation | 14 | 5
Insomnia | 2 | 2
Dizziness | 0 | 1
Akathisia | 8 | 0
Rigidity | 2 | 0
Speech disorder | 2 | 0
Handwriting change | 1 | 0
Akinesia | 8 | 0
Psychiatric
Depression | 2 | 3
Excitement | 0 | 1
Nervous | 1 | 0
Adverse behavior effect | 5 | 0
Special Senses
Visual disturbance | 4 | 0
Taste change | 1 | 0
Sensitivity of eyes to light | 1 | 0
Decrease accommodation | 4 | 1
Spots before eyes | 0 | 1
Urogenital
Impotence | 3 | 0

The following adverse event tabulation was derived from 36 children (age 2 to 12) in a 24-week open trial of pimozide in Tourette’s Disorder. Because clinical investigational experience with pimozide in Tourette’s Disorder is limited, uncommon

Body System/ Adverse Reaction | Number of Patients Experiencing Each Event (%)
 | All Events (N=36) | Drug-Related Events (N=36)
Body as a Whole
Asthenia | 9 (25.0) | 5 (13.8)
Headache | 8 (22.2) | 1 (2.7)
Gastrointestinal
Dysphagia | 1 (2.7) | 1 (2.7)
Increased Salivation | 5 (13.8) | 2 (5.5)
Musculoskeletal
Myalgia | 1 (2.7) | 1 (2.7)
Central Nervous System
Dreaming Abnormal | 1 (2.7) | 1 (2.7)
Hyperkinesia | 2 (5.5) | 1 (2.7)
Somnolence | 10 (27.7) | 9 (25.0)
Torticollis | 1 (2.7) | 1 (2.7)
Tremor, Limbs | 1 (2.7) | 1 (2.7)
Psychiatric
Adverse Behavior Effect | 10 (27.7) | 8 (22.2)
Nervous | 3 (8.3) | 2 (5.5)
Skin
Rash | 3 (8.3) | 1 (2.7)
Special Senses
Visual Disturbance | 2 (5.5) | 1 (2.7)
Cardiovascular
ECG Abnormal | 1 (2.7) | 1 (2.7)

adverse reactions may not have been detected. The physician should consider that other adverse reactions associated with antipsychotics may occur.

Other Adverse Reactions

In addition to the adverse reactions listed above, those listed below have been reported in U.S. clinical trials of pimozide in conditions other than Tourette’s Disorder.

Body as a Whole: Asthenia, chest pain, periorbital edema

Cardiovascular/Respiratory: Postural hypotension, hypotension, hypertension, tachycardia, palpitations

Gastrointestinal: Increased salivation, nausea, vomiting, anorexia, GI distress

Endocrine: Loss of libido

Metabolic/Nutritional: Weight gain, weight loss

Central Nervous System: Dizziness, tremor, parkinsonism, fainting, dyskinesia

Psychiatric: Excitement

Skin: Rash, sweating, skin irritation

Special Senses: Blurred vision, cataracts

Urogenital: Nocturia, urinary frequency

Postmarketing Reports

The following experiences were described in spontaneous postmarketing reports. These reports do not provide sufficient information to establish a clear causal relationship with the use of pimozide.

Gastrointestinal: Gingival hyperplasia in one patient

Hematologic: Hemolytic anemia

Metabolic/Nutritional: Hyponatremia

Other: Seizure

OVERDOSAGE

In general, the signs and symptoms of overdosage with pimozide would be an exaggeration of known pharmacologic effects and adverse reactions, the most prominent of which would be: 1) electrocardiographic abnormalities, 2) severe extrapyramidal reactions, 3) hypotension, 4) a comatose state with respiratory depression.
In the event of overdosage, gastric lavage, establishment of a patent airway and, if necessary, mechanically-assisted respiration are advised. Electrocardiographic monitoring should commence immediately and continue until the ECG parameters are within the normal range. Hypotension and circulatory collapse may be counteracted by use of intravenous fluids, plasma, or concentrated albumin, and vasopressor agents such as metaraminol, phenylephrine and norepinephrine.
Epinephrine should not be used. In case of severe extrapyramidal reactions, antiparkinson medication should be administered. Because of the long half-life of pimozide, patients who take an overdose should be observed for at least 4 days. As with all drugs, the physician should consider contacting a poison control center for additional information on the treatment of overdose.

DOSAGE AND ADMINISTRATION

General
The suppression of tics by pimozide tablets, USP requires a slow and gradual introduction of the drug. The patient’s dose should be carefully adjusted to a point where the suppression of tics and the relief afforded is balanced against the untoward side effects of the drug.

An ECG should be done at baseline and periodically thereafter, especially during the period of dose adjustment (see WARNINGS and PRECAUTIONS - Laboratory Tests). Periodic attempts should be made to reduce the dosage of pimozide tablets, USP to see whether or not tics persist at the level and extent first identified. In attempts to reduce the dosage of pimozide tablets, USP consideration should be given to the possibility that increases of tic intensity and frequency may represent a transient, withdrawal related phenomenon rather than a return of disease symptoms. Specifically, one to two weeks should be allowed to elapse before one concludes that an increase in tic manifestations is a function of the underlying disease syndrome rather than a response to drug withdrawal. A gradual withdrawal is recommended in any case.

Children
Reliable dose response data for the effects of pimozide tablets, USP on tic manifestation in Tourette’s Disorder patients below the age of twelve are not available.

Treatment should be initiated at a dose of 0.05 mg/kg preferably taken once at bedtime. The dose may be increased every third day to a maximum of 0.2 mg/kg not to exceed 10 mg/day. At doses above 0.05 mg/kg/day, CYP 2D6 genotyping should be performed. In poor CYP 2D6 metabolizers, pimozide tablets, USP doses should not exceed 0.05 mg/kg/day, and doses should not be increased earlier than 14 days (see PRECAUTIONS – Pharmacogenomics).

Adults
In general, treatment with pimozide tablets, USP should be initiated with a dose of 1 to 2 mg a day in divided doses. The dose may be increased thereafter every other day. Most patients are maintained at less than 0.2 mg/kg/day, or 10 mg/day, whichever is less. Doses greater than 0.2 mg/kg/day or 10 mg/day are not recommended.

At doses above 4 mg/day, CYP 2D6 genotyping should be performed. In poor CYP 2D6 metabolizers, pimozide tablets, USP doses should not exceed 4 mg/day, and doses should not be increased earlier than 14 days (see PRECAUTIONS – Pharmacogenomics).

ANIMAL PHARMACOLOGY

A chronic study in dogs indicated that pimozide caused gingival hyperplasia when administered for several months at about 5 times the maximum recommended human dose. This condition was reversible after withdrawal.

HOW SUPPLIED

Pimozide Tablets USP, 1 mg are white to off-white, uncoated round shaped tablets with debossed bisect separating "EP" and "320" on one side and other side has a single bisect. They are available in bottles of 100 (NDC 49884-347-01).

Pimozide Tablets USP, 2 mg are white to off-white, uncoated oval shaped tablets with debossed bisect separating "EP" and "321" on one side and other side has a single bisect. They are available in bottles of 100 (NDC 49884-348-01).

Store at 20° to 25°C (68° to 77°F) [See USP Controlled Room Temperature].

Pharmacist: Dispense in a tight, light-resistant container as defined in the official compendium with a child-resistant closure as required.

Rx Only

Manufactured for:
Endo USA
Malvern, PA 19355 U.S.A.
Made in India
Neutral Code: TN/DRUGS/TN00002121
© 2024 Endo, Inc. or one of its affiliates.
Revised: 08/2024